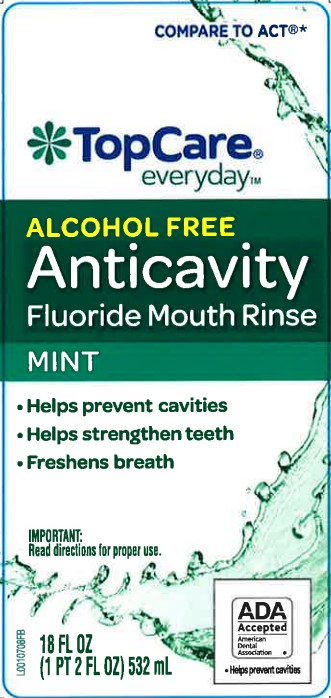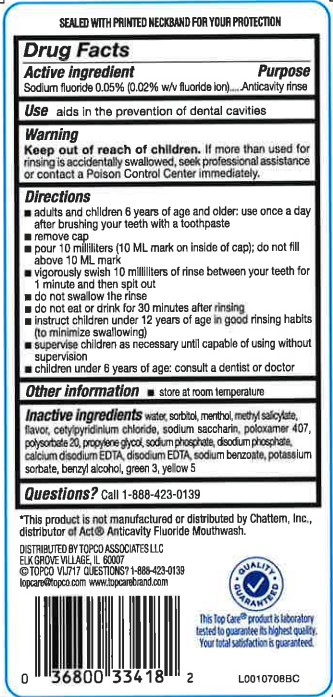 DRUG LABEL: Anticavity Fluoride Rinse
NDC: 36800-213 | Form: MOUTHWASH
Manufacturer: Topco Associates LLC
Category: otc | Type: HUMAN OTC DRUG LABEL
Date: 20260213

ACTIVE INGREDIENTS: SODIUM FLUORIDE 0.2 mg/1 mL
INACTIVE INGREDIENTS: WATER; SORBITOL; MENTHOL; METHYL SALICYLATE; CETYLPYRIDINIUM CHLORIDE; SACCHARIN SODIUM; POLOXAMER 407; POLYSORBATE 20; PROPYLENE GLYCOL; SODIUM PHOSPHATE; SODIUM PHOSPHATE, DIBASIC, MONOHYDRATE; EDETATE CALCIUM DISODIUM; EDETATE DISODIUM ANHYDROUS; SODIUM BENZOATE; POTASSIUM SORBATE; BENZYL ALCOHOL; FD&C GREEN NO. 3; FD&C YELLOW NO. 5

Top Care 213.002/213AE rev 2
Anticavity Fluoride Rinse, Mint

Tamper Evident Statement

SEALED WITH PRINTED NECKBAND FOR YOUR PROTECTION

Active ingredient

Sodium Fluoride 0.05% (0.02% w/v fluoride ion)

Purpose

Anticavity rinse

Use

aids in the prevention of dental cavities

Warning

for this product

Keep out of reach of children.

If more than used for rinsing is accidentally swallowed, seek professional assistance or contact a Poison Control Center immediately.

Directions

- adults and children 6 years of age and older: use once a day after brushing your teeth with a toothpaste.
- remove cap
- pour 10 milliliters (10 mL mark on inside of cap); do not fill above 10 mL mark
- vigorously swish 10 milliliters of rinse between your teeth for 1 minute and then spit out
- do now swallow the rinse
- do not eat or drink for 30 minutes after rinsing
- instruct children under 12 years of age in good rinsing habits (to minimize swallowing)
- supervise children as necessary until capable of using without supervision
- children under 6 years of age: consult a dentist or doctor

Other information

- store at room temperature

Inactive ingredients

water, sorbitol, menthol, methyl salicylate, flavor, cetylpyridinium chloride, sodium saccharin, poloxamer 407, polysorbate 20, propylene glycol, sodium phosphate, disodium phosphate, calcium disodium EDTA, disodium EDTA, sodium benzoate, potassium sorbate, benzyl alcohol, green 3, yellow 5

Questions?

Call 1-888-423-0139

Adverse reactions

*This product is not manufactured or distributed by Chattem, Inc., distributor of Act®Anticavity Fluoride Mouthwash.

DISTRIBUTED BY: TOCO ASSOCIATES LLC

ELK GROVE VILLAGE, IL 60007

(C) TOPCO VIJ717 QUESTIONS? 1-888-423-0139

topcare@topcare.com www.topcarebrand.com

QUALITY GUARANTEED

This Top Careproduct is laboratory tested to guarantee its highest quality.

Your total satisfaction is guaranteed.

Principal display panel

COMPARE TO ACT®*

TopCare®

everyday™

ALCOHOL FREE

Anticavity

Fluoride Mouth Rinse

MINT

- Helps prevent cavities
- Helps strengthen teeth
- Freshens breath

IMPORTANT: Read direction for proper use.

ADA Accepted

American Dental Association

- Helps prevent cavities

18 FL OZ (1 PT 2 FL OZ) 532 mL